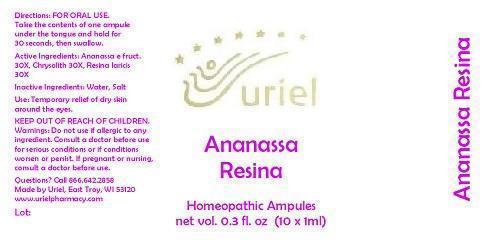 DRUG LABEL: Ananassa Resina
NDC: 48951-1032 | Form: LIQUID
Manufacturer: Uriel Pharmacy Inc.
Category: homeopathic | Type: HUMAN OTC DRUG LABEL
Date: 20140820

ACTIVE INGREDIENTS: PINEAPPLE 30 [hp_X]/1 mL; COLLOIDAL SILICON DIOXIDE 30 [hp_X]/1 mL; LARIX DECIDUA RESIN 30 [hp_X]/1 mL
INACTIVE INGREDIENTS: WATER; SODIUM CHLORIDE

Ananassa Resina

INDICATIONS AND USAGE

Directions: FOR ORAL USE.

DOSAGE AND ADMINISTRATION

Take the contents of one ampule under the tongue and hold for 30 seconds, then swallow.

ACTIVE INGREDIENT

Active Ingredients: Ananassa e fruct. 30X, Chrysolith 30X, Resina laricis 30X

Inactive Ingredients: Water, Salt

PURPOSE

Use: Temporary relief of dry skin around the eyes.

KEEP OUT OF REACH OF CHILDREN.

WARNINGS

Warnings: Do not use if allergic to any ingredient. Consult a doctor before use for serious conditions or if conditions worsen or persist. If pregnant or nursing, consult a doctor before use.

QUESTIONS

Questions? Call 866.642.2858 Made by Uriel, East Troy, WI 53120 www.urielpharmacy.com